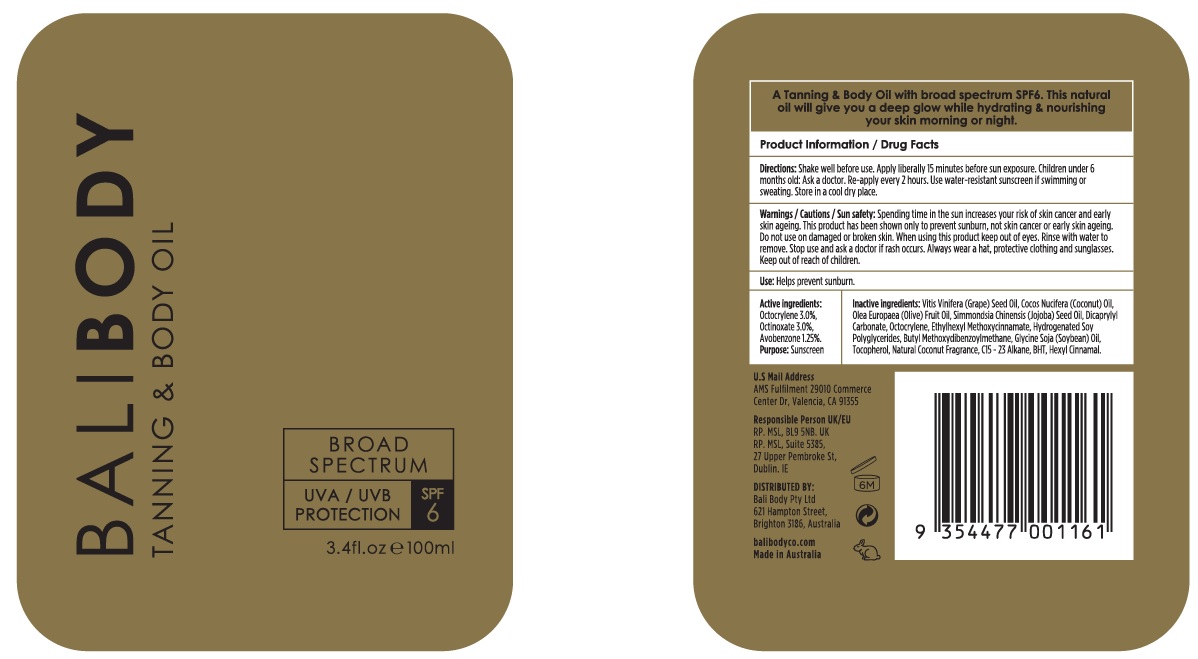 DRUG LABEL: Natural Tanning and Body Oil SPF6
NDC: 70630-0027 | Form: OIL
Manufacturer: Bali Body Pty Ltd
Category: otc | Type: HUMAN OTC DRUG LABEL
Date: 20241021

ACTIVE INGREDIENTS: OCTOCRYLENE 30 mg/1 mL; OCTINOXATE 30 mg/1 mL; AVOBENZONE 12.5 mg/1 mL
INACTIVE INGREDIENTS: GRAPE SEED OIL; COCONUT OIL; OLIVE OIL; JOJOBA OIL; DICAPRYLYL CARBONATE; SOYBEAN OIL; TOCOPHEROL; C15-23 ALKANE; BUTYLATED HYDROXYTOLUENE; .ALPHA.-HEXYLCINNAMALDEHYDE

Natural Tanning & Body Oil SPF6

Directions:

Shake well before use. Apply liberally 15 minutes before sun exposure. Children under 6 months old: Ask a doctor. Re-apply every 2 hours. Use water-resistant sunscreen if swimming or sweating. Store in a cool dry place.

Warnings / Cautions / Sun safety:

Spending time in the sun increases your risk of skin cancer or early skin ageing. This product has been shown only to prevent sunburn, not skin cancer or early skin ageing.

Do not use

on damaged or broken skin.

When using this product

keep out of eyes. Rinse with water to remove.

Stop use and ask a doctor

if rash occurs. Always wear a hat, protective clothing and sunglasses.

Use:

Helps prevent sunburn.

Active ingredients:

Octocrylene 3.0%,
Octinoxate 3.0%,
Avobenzone 1.25%.

Purpose:

Sunsreen

Inactive ingredients:

Vitis Vinifera (Grape) Seed Oil, Cocos Nucifera (Coconut) Oil,Olea Europaea (Olive) Fruit Oil, Simmondsia Chinensis (Jojoba) Seed Oil, Dicaprylyl Carbonate, Octocrylene, Ethylhexyl Methoxycinnamate, Hydrogenated Soy Polyglycerides, Butyl Methoxydibenzoylmethane, Glycine Soja (Soybean) Oil, Tocopherol, Natural Coconut Fragrance, C15-23 Alkane, BHT, Hexyl Cinnamal.